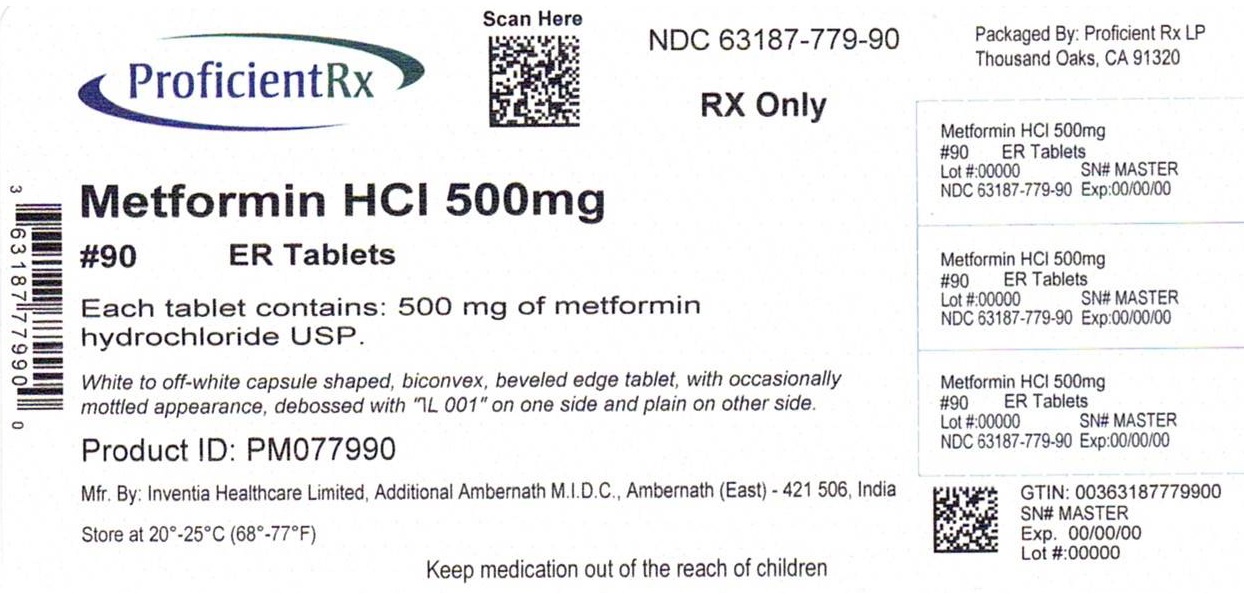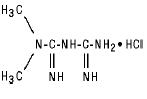 DRUG LABEL: Metformin hydrochloride
NDC: 63187-779 | Form: TABLET, EXTENDED RELEASE
Manufacturer: Proficient Rx LP
Category: prescription | Type: HUMAN PRESCRIPTION DRUG LABEL
Date: 20260101

ACTIVE INGREDIENTS: METFORMIN HYDROCHLORIDE 500 mg/1 1
INACTIVE INGREDIENTS: CARBOXYMETHYLCELLULOSE SODIUM, UNSPECIFIED; HYPROMELLOSE, UNSPECIFIED; MAGNESIUM STEARATE

Metformin Hydrochloride Extended Release Tablets USP

Rx only

DESCRIPTION

Metformin hydrochloride extended release tablets USP is an oral antihyperglycemic drug used in the management of type 2 diabetes. Metformin hydrochloride (N,N-dimethylimidodicar- bonimidic diamide hydrochloride) is not chemically or pharmacologically related to any other classes of oral antihyperglycemic agents. The structural formula is as shown:

Metformin hydrochloride is a white to off-white crystalline compound with a molecular formula of C4H11N5• HCl and a molecular weight of 165.63. Metformin hydrochloride is freely soluble in water and is practically insoluble in acetone, ether, and chloroform. The pKa of metformin is 12.4. The pH of a 1% aqueous solution of metformin hydrochloride is 6.68.

Metformin hydrochloride extended release tablets USP contain 500 mg of metformin hydrochloride USP as the active ingredient.

Metformin hydrochloride extended release tablets USP 500 mg contain the inactive ingredients sodium carboxymethyl cellulose, hypromellose and magnesium stearate. Metformin hydrochloride extended release tablets USP 500 mg meets USP dissolution Test 3.

System Components and Performance- Metformin hydrochloride extended release tablets USP comprises a swellable matrix system. In the aqueous gastrointestinal (GI) environment, the dosage form swells remarkably thereby increasing in size and geometry from where drug is released slowly by a process of diffusion through the gel matrix that is essentially independent of pH. The hydrated polymer system is not rigid and is expected to be broken up by normal peristalsis in the GI tract. The biologically inert components of the tablet may occasionally remain intact during GI transit and will be eliminated in the feces as a soft, hydrated mass.

Mechanism of Action

Metformin is an antihyperglycemic agent which improves glucose tolerance in patients with type 2 diabetes, lowering both basal and postprandial plasma glucose. Its pharmacologic mechanisms of action are different from other classes of oral antihyperglycemic agents. Metformin decreases hepatic glucose production, decreases intestinal absorption of glucose, and improves insulin sensitivity by increasing peripheral glucose uptake and utilization. Unlike sulfonylureas, metformin does not produce hypoglycemia in either patients with type 2 diabetes or normal subjects (except in special circumstances, see Error! Hyperlink reference not valid.) and does not cause hyperinsulinemia. With metformin therapy, insulin secretion remains unchanged while fasting insulin levels and day-long plasma insulin response may actually decrease.

Pharmacokinetics

Absorption and Bioavailability

Following a single oral dose of metformin hydrochloride extended release tablets USP, Cmax is achieved with a median value of 7 hours and a range of 4 hours to 8 hours.
Peak plasma levels are approximately 20% lower compared to the same dose of metformin hydrochloride tablets however, the extent of absorption (as measured by AUC) is similar to metformin hydrochloride tablets.

At steady state, the AUC and Cmax are less than dose proportional for metformin hydrochloride extended release tablets USP within the range of 500 mg to 2000 mg administered once daily. Peak plasma levels are approximately 0.6, 1.1, 1.4, and 1.8 μg/mL for 500, 1000, 1500, and 2000 mg once-daily doses, respectively. The extent of metformin absorption (as measured by AUC) from metformin hydrochloride extended release tablets USP at a 2000 mg once-daily dose is similar to the same total daily dose administered as metformin hydrochloride tablets 1000 mg twice daily. After repeated administration of metformin hydrochloride extended release tablets USP, metformin did not accumulate in plasma.

Within-subject variability in Cmax and AUC of metformin from metformin hydrochloride extended release tablets USP is comparable to that with metformin hydrochloride tablets.

Although the extent of metformin absorption (as measured by AUC) from the metformin hydrochloride extended release tablet USP increased by approximately 50% when given with food, there was no effect of food on Cmax and Tmax of metformin. Both high and low fat meals had the same effect on the pharmacokinetics of metformin hydrochloride extended release tablets USP.

Distribution

The apparent volume of distribution (V/F) of metformin following single oral doses of metformin hydrochloride 850 mg tablets averaged 654 ± 358 L. Metformin is negligibly bound to plasma proteins, in contrast to sulfonylureas, which are more than 90% protein bound. Metformin partitions into erythrocytes, most likely as a function of time. At usual clinical doses and dosing schedules of metformin hydrochloride, steady state plasma concentrations of metformin are reached within 24 to 48 hours and are generally LESS THAN 1 μg/mL. During controlled clinical trials of metformin hydrochloride tablets, maximum metformin plasma levels did not exceed 5 μg/mL, even at maximum doses.

Metabolism and Elimination

Intravenous single-dose studies in normal subjects demonstrate that metformin is excreted unchanged in the urine and does not undergo hepatic metabolism (no metabolites have been identified in humans) nor biliary excretion. Renal clearance (see Error! Hyperlink reference not valid.) is approximately 3.5 times greater than creatinine clearance, which indicates that tubular secretion is the major route of metformin elimination. Following oral administration, approximately 90% of the absorbed drug is eliminated via the renal route within the first 24 hours, with a plasma elimination half-life of approximately 6.2 hours. In blood, the elimination half-life is approximately 17.6 hours, suggesting that the erythrocyte mass may be a compartment of distribution.

Special Populations

Patients with Type 2 Diabetes

In the presence of normal renal function, there are no differences between single- or multiple-dose pharmacokinetics of metformin between patients with type 2 diabetes and normal subjects (see Error! Hyperlink reference not valid.), nor is there any accumulation of metformin in either group at usual clinical doses.

The pharmacokinetics of metformin hydrochloride extended release tablets USP in patients with type 2 diabetes are comparable to those in healthy normal adults.

Renal Insufficiency

In patients with decreased renal function (based on measured creatinine clearance), the plasma and blood half-life of metformin is prolonged and the renal clearance is decreased in proportion to the decrease in creatinine clearance (see Error! Hyperlink reference not valid.; also see Error! Hyperlink reference not valid.).

Hepatic Insufficiency

No pharmacokinetic studies of metformin have been conducted in patients with hepatic insufficiency.

Geriatrics

Limited data from controlled pharmacokinetic studies of metformin hydrochloride in healthy elderly subjects suggest that total plasma clearance of metformin is decreased, the half-life is prolonged, and Cmax is increased, compared to healthy young subjects. From these data, it appears that the change in metformin pharmacokinetics with aging is primarily accounted for by a change in renal function (see Error! Hyperlink reference not valid.). Metformin hydrochloride treatment should not be initiated in patients ≥ 80 years of age unless measurement of creatinine clearance demonstrates that renal function is not reduced (see Error! Hyperlink reference not valid.and Error! Hyperlink reference not valid.).

Table 1: Select Mean (±S.D.) Metformin Pharmacokinetic Parameters Following Single or
Multiple Oral Doses of Metformin Hydrochloride.
Subject Groups: Metformin Hydrochloride dosea (number of subjects) | Cmaxb (μg/mL) | Tmaxc (hrs) | Renal Clearance (mL/min)
Healthy, nondiabetic adults: 500 mg single dose (24) 850 mg single dose (74)d 850 mg three times daily for 19 dosese (9) | 1.03 (±0.33) 1.60 (±0.38) 2.01 (±0.42) | 2.75 (±0.81) 2.64 (±0.82) 1.79 (±0.94) | 600 (±132) 552 (±139) 642 (±173)
Adults with type 2 diabetes: 850 mg single dose (23) 850 mg three times daily for 19 dosese (9) | 1.48 (±0.5) 1.90 (±0.62) | 3.32 (±1.08) 2.01 (±1.22) | 491 (±138) 550 (±160)
Elderlyf, healthy nondiabetic adults: 850 mg single dose (12) | 2.45 (±0.70) | 2.71 (±1.05) | 412 (±98)
Renal-impaired adults: 850 mg single dose Mild (CLcrg 61-90 mL/min) (5) Moderate (CLcr 31-60 mL/min) (4) Severe (CLcr 10-30 mL/min) (6) | 1.86 (±0.52) 4.12 (±1.83) 3.93 (±0.92) | 3.20 (±0.45) 3.75 (±0.50) 4.01 (±1.10) | 384 (±122) 108 (±57) 130 (±90)
aAll doses given fasting except the first 18 doses of the multiple dose studies
bPeak plasma concentration
cTime to peak plasma concentration
dCombined results (average means) of five studies: mean age 32 years (range 23-59 years)
eKinetic study done following dose 19, given fasting
fElderly subjects, mean age 71 years (range 65-81 years)
gCLcr = creatinine clearance normalized to body surface area of 1.73 m^2

Pediatrics

After administration of a single oral metformin hydrochloride 500 mg tablet with food, geometric mean metformin Cmax and AUC differed less than 5% between pediatric type 2 diabetic patients (12 to 16 years of age) and gender- and weight-matched healthy adults (20 to 45 years of age), all with normal renal function.

Gender

Metformin pharmacokinetic parameters did not differ significantly between normal subjects and patients with type 2 diabetes when analyzed according to gender (males = 19, females = 16). Similarly, in controlled clinical studies in patients with type 2 diabetes, the antihyperglycemic effect of metformin hydrochloride tablets was comparable in males and females.

Race

No studies of metformin pharmacokinetic parameters according to race have been performed. In controlled clinical studies of metformin hydrochloride tablets in patients with type 2 diabetes, the antihyperglycemic effect was comparable in whites (n=249), blacks (n=51), and Hispanics (n=24).

Clinical Studies
Metformin Hydrochloride Extended Release Tablets USP

A 24-week, double-blind, placebo-controlled study of metformin hydrochloride extended release tablets USP , taken once daily with the evening meal, was conducted in patients with type 2 diabetes who had failed to achieve glycemic control with diet and exercise (HbA1c 7.0%-10.0%, FPG 126-270 mg/dL). Patients entering the study had a mean baseline HbA1c of 8.0% and a mean baseline FPG of 176 mg/dL. After 12 weeks treatment, mean HbA1c had increased from baseline by 0.1% and mean FPG decreased from baseline by 2 mg/dL in the placebo group, compared with a decrease in mean HbA1c had increased from baseline by 0.1% and mean FPG decreased from baseline by 2 mg/dL in the placebo group, compared with a decrease in mean HbA1c of 0.6% and a decrease in mean FPG of 23 mg/dL in patients treated with metformin hydrochloride extended release tablets USP 1000 mg once daily. Subsequently, the treatment dose was increased to 1500 mg once daily if HbA1c was ≥7.0% but <8.0% (patients with HbA1c ≥8.0% were discontinued from the study). At the final visit (24-week), mean HbA1c had increased 0.2% from baseline in placebo patients and decreased 0.6% with metformin hydrochloride extended release tablets USP.

A 16-week, double-blind, placebo-controlled, dose-response study of metformin hydrochloride extended release tablets USP, taken once daily with the evening meal or twice daily with meals, was conducted in patients with type 2 diabetes who had failed to achieve glycemic control with diet and exercise (HbA1c 7.0%-11.0%, FPG 126-280 mg/dL). Changes in glycemic control and body weight are shown in Table 6.

Table 6: Summary of Mean Changes from Baseline* in HbA1c, Fasting Plasma Glucose, and Body Weight at Final Visit (16-week study)
 | Metformin Hydrochloride Extended Release Tablets USP
 | 500 mg Once Daily | 1000 mg Once Daily | 1500 mg Once Daily | 2000 mg Once Daily | 1000 mg Twice Daily | Placebo
Hemoglobin A1c (%) Baseline Change at FINAL VISIT p-valuea | (n=115) 8.2 -0.4 <0.001 | (n=115) 8.4 -0.6 <0.001 | (n=111) 8.3 -0.9 <0.001 | (n=125) 8.4 -0.8 <0.001 | (n=112) 8.4 -1.1 <0.001 | (n=111) 8.4 0.1 -
FPG (mg/dL) Baseline Change at FINAL VISIT p-valuea | (n=126) 182.7 -15.2 <0.001 | (n=118) 183.7 -19.3 <0.001 | (n=120) 178.9 -28.5 <0.001 | (n=132) 181.0 -29.9 <0.001 | (n=122) 181.6 -33.6 <0.001 | (n=113) 179.6 7.6 -
Body Weight(lbs) Baseline Change at FINAL VISIT p-valuea | (n=125) 192.9 -1.3 NS** | (n=119) 191.8 -1.3 NS** | (n=117) 188.3 -0.7 NS** | (n=131) 195.4 -1.5 NS** | (n=119) 192.5 -2.2 NS** | (n=113) 194.3 -1.8 -
* All patients on diet therapy at Baseline
aAll comparisons versus Placebo
** Not statistically significant

Compared with placebo, improvement in glycemic control was seen at all dose levels of metformin hydrochloride extended release tablets USP and treatment was not associated with any significant change in weight (see Error! Hyperlink reference not valid. for dosing recommendations for metformin hydrochloride extended release tablets USP).

A 24-week, double-blind, randomized study of metformin hydrochloride extended release tablets USP, taken once daily with the evening meal, and metformin hydrochloride tablets, taken twice daily (with breakfast and evening meal), was conducted in patients with type 2 diabetes who had been treated with metformin hydrochloride tablets 500 mg twice daily for at least 8 weeks prior to study entry.

The metformin hydrochloride tablets dose had not necessarily been titrated to achieve a specific level of glycemic control prior to study entry. Patients qualified for the study if HbA1c was ≤8.5% and FPG was ≤200 mg/dL. Changes in glycemic control and body weight are shown in Table 7.

Table 7: Summary of Mean Changes from Baseline* in HbA1c, Fasting Plasma Glucose, and Body Weight at Week 12 and at Final Visit (24-week study)
 | Metformin Hydrochloride Tablets | Metformin Hydrochloride Extended Release Tablets USP
 | 500 mg Twice Daily | 1000 mg Once Daily | 1500 mg Once Daily
Hemoglobin A1c (%) Baseline Change at 12 Weeks (95% CI) Change at FINAL VISIT (95% CI) | (n=67) 7.06 0.14 (-0.03, 0.31) 0.14a (-0.04, 0.31) | (n=72) 6.99 0.23 (0.10, 0.36) 0.27 (0.11, 0.43) | (n=66) 7.02 0.04 (-0.08, 0.15) 0.13 (-0.02, 0.28)
FPG (mg/dL) Baseline Change at 12 Weeks (95% CI) Change at FINAL VISIT (95% CI) | (n=69) 127.2 12.9 (6.5, 19.4) 14.0 (7.0, 21.0) | (n=72) 131.0 9.5 (4.4, 14.6) 11.5 (4.4, 18.6) | (n=70) 131.4 3.7 (-0.4, 7.8) 7.6 (1.0, 14.2)
Body Weight(lbs) Baseline Change at 12 Weeks (95% CI) Change at FINAL VISIT (95% CI) | (n=71) 210.3 0.4 (-0.4, 1.5) 0.9 (-0.4, 2.2) | (n=74) 202.8 0.9 (0.0, 2.0) 1.1 (-0.2, 2.4) | (n=71) 192.7 0.7 (-0.4, 1.8) 0.9 (-0.4, 2.0)
* All patients on metformin hydrochloride tablets 500 mg twice daily at Baseline
a n=68

After 12 weeks of treatment, there was an increase in mean HbA1c in all groups; in the metformin hydrochloride extended release tablets USP 1000 mg group, the increase from baseline of 0.23% was statistically significant (see Error! Hyperlink reference not valid.).

Changes in lipid parameters in the previously described placebo-controlled dose-response study of metformin hydrochloride extended release tablets USP are shown in Table 8.

Table 8: Summary of Mean Percent Changes from Baseline* in Major Lipid Variables at Final Visit (16-week study)
 | Metformin Hydrochloride Extended Release Tablets USP
 | 500 mg Once Daily | 1000 mg Once Daily | 1500 mg Once Daily | 2000 mg Once Daily | 1000 mg Twice Daily | Placebo
Total Cholesterol (mg/dL) Baseline Mean % Change at FINAL VISIT | (n=120) 210.3 1.0% | (n=113) 218.1 1.7% | (n=110) 214.6 0.7% | (n=126) 204.4 -1.6% | (n=117) 208.2 -2.6% | (n=110) 208.6 2.6%
Total Triglycerides (mg/dL) Baseline Mean % Change at FINAL VISIT | (n=120) 220.2 14.5% | (n=113) 211.9 9.4% | (n=110) 198.0 15.1% | (n=126) 194.2 14.9% | (n=117) 179.0 9.4% | (n=110) 211.7 10.9%
LDL-Cholesterol (mg/dL) Baseline Mean % Change at FINAL VISIT | (n=119) 131.0 -1.4% | (n=113) 134.9 -1.6% | (n=109) 135.8 -3.5% | (n=126) 125.8 -3.3% | (n=117) 131.4 -5.5% | (n=107) 131.9 3.2%
HDL-Cholesterol (mg/dL) Baseline Mean % Change at FINAL VISIT | (n=120) 40.8 6.2% | (n=108) 41.6 8.6% | (n=108) 40.6 5.5% | (n=125) 40.2 6.1% | (n=117) 42.4 7.1% | (n=108) 39.4 5.8%
*All patients on diet therapy at Baseline

Changes in lipid parameters in the previously described study of metformin hydrochloride tablets and metformin hydrochloride extended release tablets USP are shown in Table 9.

Table 9: Summary of Mean Percent Changes from Baseline* in Major Lipid Variables at Final Visit (24-week study)
 | Metformin Hydrochloride Tablets | Metformin Hydrochloride Extended Release Tablets USP
 | 500 mg Twice Daily | 1000 mg Once Daily | 1500 mg Once Daily
Total Cholesterol (mg/dL) Baseline Mean % Change at FINAL VISIT | (n=68) 199.0 0.1% | (n=70) 201.9 1.3% | (n=66) 201.6 0.1%
Total Triglycerides (mg/dL) Baseline Mean % Change at FINAL VISIT | (n=68) 178.0 6.3% | (n=70) 169.2 25.3% | (n=66) 206.8 33.4%
LDL-Cholesterol (mg/dL) Baseline Mean %Change at FINAL VISIT | (n=68) 122.1 -1.3% | (n=70) 126.2 -3.3% | (n=66) 115.7 -3.7%
HDL-Cholesterol (mg/dL) Baseline Mean % Change at FINAL VISIT | (n=68) 41.9 4.8% | (n=70) 41.7 1.0% | (n=65) 44.6 -2.1%
*All patients on metformin hydrochloride tablet 500 mg twice daily at Baseline

INDICATIONS AND USAGE

Metformin hydrochloride extended release tablets USP are indicated as an adjunct to diet and exercise to improve glycemic control in adults with type 2 diabetes mellitus.

CONTRAINDICATIONS

Metformin hydrochloride are contraindicated in patients with:

1. Renal disease or renal dysfunction (e.g., as suggested by serum creatinine levels ≥1.5 mg/dL [males], ≥1.4 mg/dL [females] or abnormal creatinine clearance) which may also result from conditions such as cardiovascular collapse (shock), acute myocardial infarction, and septicemia (see Error! Hyperlink reference not valid. and Error! Hyperlink reference not valid.).
2. Known hypersensitivity to metformin hydrochloride.
3. Acute or chronic metabolic acidosis, including diabetic ketoacidosis, with or without coma. Diabetic ketoacidosis should be treated with insulin.

Metformin hydrochloride should be temporarily discontinued in patients undergoing radiologic studies involving intravascular administration of iodinated contrast materials, because use of such products may result in acute alteration of renal function. (See also Error! Hyperlink reference not valid.)

BOXED WARNING

Lactic Acidosis:

Lactic acidosis is a rare, but serious, metabolic complication that can occur due to metformin accumulation during treatment with metformin hydrochloride extended release tablets USP when it occurs, it is fatal in approximately 50% of cases. Lactic acidosis may also occur in association with a number of pathophysiologic conditions, including diabetes mellitus, and whenever there is significant tissue hypoperfusion and hypoxemia. Lactic acidosis is characterized by elevated blood lactate levels (>5 mmol/L), decreased blood pH, electrolyte disturbances with an increased anion gap, and an increased lactate/pyruvate ratio. When metformin is implicated as the cause of lactic acidosis, metformin plasma levels >5 μg/mL are generally found.

The reported incidence of lactic acidosis in patients receiving metformin hydrochloride is very low (approximately 0.03 cases/1000 patient-years, with approximately 0.015 fatal cases/1000 patient-years). In more than 20,000 patient-years exposure to metformin in clinical trials, there were no reports of lactic acidosis. Reported cases have occurred primarily in diabetic patients with significant renal insufficiency, including both intrinsic renal disease and renal hypoperfusion, often in the setting of multiple concomitant medical/surgical problems and multiple concomitant medications. Patients with congestive heart failure requiring pharmacologic management, in particular those with unstable or acute congestive heart failure who are at risk of hypoperfusion and hypoxemia, are at increased risk of lactic acidosis. The risk of lactic acidosis increases with the degree of renal dysfunction and the patient's age. The risk of lactic acidosis may, therefore, be significantly decreased by regular monitoring of renal function in patients taking metformin hydrochloride extended release tablets USP and by use of the minimum effective dose of metformin hydrochloride extended release tablets USP. In particular, treatment of the elderly should be accompanied by careful monitoring of renal function. Metformin hydrochloride extended release tablets USP treatment should not be initiated in patients ≥80 years of age unless measurement of creatinine clearance demonstrates that renal function is not reduced, as these patients are more susceptible to developing lactic acidosis. In addition, metformin hydrochloride should be promptly withheld in the presence of any condition associated with hypoxemia, dehydration, or sepsis. Because impaired hepatic function may significantly limit the ability to clear lactate, metformin hydrochloride should generally be avoided in patients with clinical or laboratory evidence of hepatic disease. Patients should be cautioned against excessive alcohol intake, either acute or chronic, when taking metformin hydrochloride extended release tablets USP, since alcohol potentiates the effects of metformin hydrochloride on lactate metabolism. In addition, metformin hydrochloride should be temporarily discontinued prior to any intravascular radiocontrast study and for any surgical procedure (see also Error! Hyperlink reference not valid.).

The onset of lactic acidosis often is subtle, and accompanied only by nonspecific symptoms such as malaise, myalgias, respiratory distress, increasing somnolence, and nonspecific abdominal distress. There may be associated hypothermia, hypotension, and resistant bradyarrhythmias with more marked acidosis. The patient and the patient's physician must be aware of the possible importance of such symptoms and the patient should be instructed to notify the physician immediately if they occur (see also Error! Hyperlink reference not valid.). Metformin hydrochloride should be withdrawn until the situation is clarified. Serum electrolytes, ketones, blood glucose, and if indicated, blood pH, lactate levels, and even blood metformin levels may be useful. Once a patient is stabilized on any dose level of metformin hydrochloride extended release tablets USP, gastrointestinal symptoms, which are common during initiation of therapy, are unlikely to be drug related. Later occurrence of gastrointestinal symptoms could be due to lactic acidosis or other serious disease.

Levels of fasting venous plasma lactate above the upper limit of normal but less than 5 mmol/L in patients taking metformin hydrochloride extended release tablets USP do not necessarily indicate impending lactic acidosis and may be explainable by other mechanisms, such as poorly controlled diabetes or obesity, vigorous physical activity, or technical problems in sample handling. (See also Error! Hyperlink reference not valid.).

Lactic acidosis should be suspected in any diabetic patient with metabolic acidosis lacking evidence of ketoacidosis (ketonuria and ketonemia).

Lactic acidosis is a medical emergency that must be treated in a hospital setting. In a patient with lactic acidosis who is taking metformin hydrochloride extended release tablets USP, the drug should be discontinued immediately and general supportive measures promptly instituted. Because metformin hydrochloride is dialyzable (with a clearance of up to 170 mL/min under good hemodynamic conditions), prompt hemodialysis is recommended to correct the acidosis and remove the accumulated metformin. Such management often results in prompt reversal of symptoms and recovery. (See also Error! Hyperlink reference not valid. and Error! Hyperlink reference not valid.).

General

Macrovascular Outcomes - There have been no clinical studies establishing conclusive evidence of macrovascular risk reduction with metformin hydrochloride extended release tablets USP or any other anti-diabetic drug.

Monitoring of renal function - Metformin is known to be substantially excreted by the kidney, and the risk of metformin accumulation and lactic acidosis increases with the degree of impairment of renal function. Thus, patients with serum creatinine levels above the upper limit of normal for their age should not receive metformin hydrochloride extended release tablets USP. In patients with advanced age, metformin hydrochloride should be carefully titrated to establish the minimum dose for adequate glycemic effect, because aging is associated with reduced renal function. In elderly patients, particularly those ≥80 years of age, renal function should be monitored regularly and, generally, metformin hydrochloride should not be titrated to the maximum dose (see Error! Hyperlink reference not valid.and Error! Hyperlink reference not valid.).

Before initiation of metformin hydrochloride extended release tablets USP tablets therapy and at least annually thereafter, renal function should be assessed and verified as normal. In patients in whom development of renal dysfunction is anticipated, renal function should be assessed more frequently and metformin hydrochloride extended release tablets USP discontinued if evidence of renal impairment is present.

Use of concomitant medications that may affect renal function or metformin disposition - Concomitant medication(s) that may affect renal function or result in significant hemodynamic change or may interfere with the disposition of metformin, such as cationic drugs that are eliminated by renal tubular secretion (see Error! Hyperlink reference not valid.), should be used with caution.

Radiologic studies involving the use of intravascular iodinated contrast materials (for example, intravenous urogram, intravenous cholangiography, angiography, and computed tomography (CT) scans with intravascular contrast materials) - Intravascular contrast studies with iodinated materials can lead to acute alteration of renal function and have been associated with lactic acidosis in patients receiving metformin (see Error! Hyperlink reference not valid.). Therefore, in patients in whom any such study is planned, metformin hydrochloride extended release tablets USP should be temporarily discontinued at the time of or prior to the procedure, and withheld for 48 hours subsequent to the procedure and reinstituted only after renal function has been re-evaluated and found to be normal.

Hypoxic states - Cardiovascular collapse (shock) from whatever cause, acute congestive heart failure, acute myocardial infarction and other conditions characterized by hypoxemia have been associated with lactic acidosis and may also cause prerenal azotemia. When such events occur in patients on metformin hydrochloride extended release tablets USP therapy, the drug should be promptly discontinued.

Surgical procedures - Metformin hydrochloride extended release tablets USP therapy should be temporarily suspended for any surgical procedure (except minor procedures not associated with restricted intake of food and fluids) and should not be restarted until the patient's oral intake has resumed and renal function has been evaluated as normal.

Alcohol intake - Alcohol is known to potentiate the effect of metformin on lactate metabolism. Patients, therefore, should be warned against excessive alcohol intake, acute or chronic, while receiving metformin hydrochloride extended release tablets USP.

Impaired hepatic function - Since impaired hepatic function has been associated with some cases of lactic acidosis, metformin hydrochloride should generally be avoided in patients with clinical or laboratory evidence of hepatic disease.

Vitamin B12 levels - In controlled clinical trials of metformin hydrochloride tablets of 29 weeks duration, a decrease to subnormal levels of previously normal serum vitamin B12 levels, without clinical manifestations, was observed in approximately 7% of patients. Such decrease, possibly due to interference with B12 absorption from the B12-intrinsic factor complex, is, however, very rarely associated with anemia and appears to be rapidly reversible with discontinuation of metformin hydrochloride tablets or vitamin B12 supplementation. Measurement of hematologic parameters on an annual basis is advised in patients on metformin hydrochloride extended release tablets USP and any apparent abnormalities should be appropriately investigated and managed (see Error! Hyperlink reference not valid.).

Certain individuals (those with inadequate vitamin B12 or calcium intake or absorption) appear to be predisposed to developing subnormal vitamin B12 levels. In these patients, routine serum vitamin B12 measurements at two- to three year intervals may be useful.

Change in clinical status of patients with previously controlled type 2 diabetes - A patient with type 2 diabetes previously well controlled on metformin hydrochloride extended release tablets USP who develops laboratory abnormalities or clinical illness (especially vague and poorly defined illness) should be evaluated promptly for evidence of ketoacidosis or lactic acidosis. Evaluation should include serum electrolytes and ketones, blood glucose and, if indicated, blood pH, lactate, pyruvate, and metformin levels. If acidosis of either form occurs, metformin hydrochloride extended release tablets USP must be stopped immediately and other appropriate corrective measures initiated (see also Error! Hyperlink reference not valid.).

Hypoglycemia - Hypoglycemia does not occur in patients receiving metformin hydrochloride extended release tablets USP alone under usual circumstances of use, but could occur when caloric intake is deficient, when strenuous exercise is not compensated by caloric supplementation, or during concomitant use with other glucose-lowering agents (such as sulfonylureas and insulin) or ethanol.

Elderly, debilitated, or malnourished patients, and those with adrenal or pituitary insufficiency or alcohol intoxication are particularly susceptible to hypoglycemic effects. Hypoglycemia may be difficult to recognize in the elderly, and in people who are taking beta-adrenergic blocking drugs.

Loss of control of blood glucose - When a patient stabilized on any diabetic regimen is exposed to stress such as fever, trauma, infection, or surgery, a temporary loss of glycemic control may occur. At such times, it may be necessary to withhold metformin hydrochloride extended release tablets USP and temporarily administer insulin. Metformin hydrochloride extended release tablets USP may be reinstituted after the acute episode is resolved.

The effectiveness of oral antidiabetic drugs in lowering blood glucose to a targeted level decreases in many patients over a period of time. This phenomenon, which may be due to progression of the underlying disease or to diminished responsiveness to the drug, is known as secondary failure, to distinguish it from primary failure in which the drug is ineffective during initial therapy. Should secondary failure occur with either metformin hydrochloride extended release tablets USP or sulfonylurea monotherapy, combined therapy with metformin hydrochloride extended release tablets USP and sulfonylurea may result in a response. Should secondary failure occur with combined metformin hydrochloride extended release tablets USP /sulfonylurea therapy, it may be necessary to consider therapeutic alternatives including initiation of insulin therapy.

Information for Patients

Patients should be informed of the potential risks and benefits of metformin hydrochloride extended release tablets USP and of alternative modes of therapy. They should also be informed about the importance of adherence to dietary instructions, of a regular exercise program, and of regular testing of blood glucose, glycosylated hemoglobin, renal function, and hematologic parameters.

The risks of lactic acidosis, its symptoms, and conditions that predispose to its development, as noted in the Error! Hyperlink reference not valid. and Error! Hyperlink reference not valid. sections, should be explained to patients. Patients should be advised to discontinue metformin hydrochloride extended release tablets USP immediately and to promptly notify their health practitioner if unexplained hyperventilation, myalgia, malaise, unusual somnolence, or other nonspecific symptoms occur. Once a patient is stabilized on any dose level of metformin hydrochloride extended release tablets USP, gastrointestinal symptoms, which are common during initiation of metformin therapy, are unlikely to be drug related. Later occurrence of gastrointestinal symptoms could be due to lactic acidosis or other serious disease.

Patients should be counselled against excessive alcohol intake, either acute or chronic, while receiving metformin hydrochloride extended release tablets USP.

Metformin hydrochloride extended release tablets USP alone does not usually cause hypoglycemia, although it may occur when metformin hydrochloride extended release tablets USP is used in conjunction with oral sulfonylureas and insulin. When initiating combination therapy, the risks of hypoglycemia, its symptoms and treatment, and conditions that predispose to its development should be explained to patients and responsible family members. (See Error! Hyperlink reference not valid. printed below.)

Patients should be informed that metformin hydrochloride extended release tablets USP must be swallowed whole and not crushed or chewed, and that the inactive ingredients may occasionally be eliminated in the feces as a soft mass that may resemble the original tablet.

Laboratory Tests

Response to all diabetic therapies should be monitored by periodic measurements of fasting blood glucose and glycosylated hemoglobin levels, with a goal of decreasing these levels toward the normal range. During initial dose titration, fasting glucose can be used to determine the therapeutic response. Thereafter, both glucose and glycosylated hemoglobin should be monitored. Measurements of glycosylated hemoglobin may be especially useful for evaluating long-term control (see also Error! Hyperlink reference not valid.).

Initial and periodic monitoring of hematologic parameters (e.g., hemoglobin/hematocrit and red blood cell indices) and renal function (serum creatinine) should be performed, at least on an annual basis. While megaloblastic anemia has rarely been seen with metformin hydrochloride therapy, if this is suspected, vitamin B12 deficiency should be excluded.

DRUG INTERACTIONS

Drug Interactions (Clinical Evaluation of Drug Interactions Conducted with Metformin Hydrochloride Tablets)

Glyburide - In a single-dose interaction study in type 2 diabetes patients, coadministration of metformin and glyburide did not result in any changes in either metformin pharmacokinetics or pharmacodynamics. Decreases in glyburide AUC and Cmax were observed, but were highly variable. The single-dose nature of this study and the lack of correlation between glyburide blood levels and pharmacodynamic effects, makes the clinical significance of this interaction uncertain (see Error! Hyperlink reference not valid.).

Furosemide - A single-dose, metformin-furosemide drug interaction study in healthy subjects demonstrated that pharmacokinetic parameters of both compounds were affected by coadministration. Furosemide increased the metformin plasma and blood Cmax by 22% and blood AUC by 15%, without any significant change in metformin renal clearance. When administered with metformin, the Cmax and AUC of furosemide were 31% and 12% smaller, respectively, than when administered alone, and the terminal half-life was decreased by 32%, without any significant change in furosemide renal clearance. No information is available about the interaction of metformin and furosemide when coadministered chronically.

Nifedipine - A single-dose, metformin-nifedipine drug interaction study in normal healthy volunteers demonstrated that coadministration of nifedipine increased plasma metformin Cmax and AUC by 20% and 9%, respectively, and increased the amount excreted in the urine. Tmax and half-life were unaffected. Nifedipine appears to enhance the absorption of metformin. Metformin had minimal effects on nifedipine.

Cationic drugs - Cationic drugs (e.g., amiloride, digoxin, morphine, procainamide, quinidine, quinine, ranitidine, triamterene, trimethoprim, or vancomycin) that are eliminated by renal tubular secretion theoretically have the potential for interaction with metformin by competing for common renal tubular transport systems. Such interaction between metformin and oral cimetidine has been observed in normal healthy volunteers in both single- and multiple-dose, metformin-cimetidine drug interaction studies, with a 60% increase in peak metformin plasma and whole blood concentrations and a 40% increase in plasma and whole blood metformin AUC. There was no change in elimination half-life in the single-dose study. Metformin had no effect on cimetidine pharmacokinetics. Although such interactions remain theoretical (except for cimetidine), careful patient monitoring and dose adjustment of metformin hydrochloride extended release tablets USP and/or the interfering drug is recommended in patients who are taking cationic medications that are excreted via the proximal renal tubular secretory system.

Other - Certain drugs tend to produce hyperglycemia and may lead to loss of glycemic control. These drugs include the thiazides and other diuretics, corticosteroids, phenothiazines, thyroid products, estrogens, oral contraceptives, phenytoin, nicotinic acid, sympathomimetics, calcium channel blocking drugs, and isoniazid. When such drugs are administered to a patient receiving metformin hydrochloride extended release tablets USP, the patient should be closely observed for loss of blood glucose control. When such drugs are withdrawn from a patient receiving metformin hydrochloride extended release tablets USP, the patient should be observed closely for hypoglycemia.

In healthy volunteers, the pharmacokinetics of metformin and propranolol, and metformin and ibuprofen were not affected when coadministered in single-dose interaction studies.

Metformin is negligibly bound to plasma proteins and is, therefore, less likely to interact with highly protein-bound drugs such as salicylates, sulfonamides, chloramphenicol, and probenecid, as compared to the sulfonylureas, which are extensively bound to serum proteins.

Carcinogenesis, Mutagenesis, Impairment of Fertility

Long-term carcinogenicity studies have been performed in rats (dosing duration of 104 weeks) and mice (dosing duration of 91 weeks) at doses up to and including 900 mg/kg/day and 1500 mg/kg/day, respectively.

These doses are both approximately four times the maximum recommended human daily dose of 2000 mg based on body surface area comparisons. No evidence of carcinogenicity with metformin was found in either male or female mice. Similarly, there was no tumorigenic potential observed with metformin in male rats. There was, however, an increased incidence of benign stromal uterine polyps in female rats treated with 900 mg/kg/day.

There was no evidence of a mutagenic potential of metformin in the following in vitro tests: Ames test (S. typhimurium), gene mutation test (mouse lymphoma cells), or chromosomal aberrations test (human lymphocytes). Results in the in vivo mouse micronucleus test were also negative.

Fertility of male or female rats was unaffected by metformin when administered at doses as high as 600 mg/kg/day, which is approximately three times the maximum recommended human daily dose based on body surface area comparisons.

Pregnancy

Teratogenic Effects: Pregnancy Category B

Recent information strongly suggests that abnormal blood glucose levels during pregnancy are associated with a higher incidence of congenital abnormalities. Most experts recommend that insulin be used during pregnancy to maintain blood glucose levels as close to normal as possible. Because animal reproduction studies are not always predictive of human response, metformin hydrochloride should not be used during pregnancy unless clearly needed.

There are no adequate and well-controlled studies in pregnant women with metformin hydrochloride extended release tablets USP. Metformin was not teratogenic in rats and rabbits at doses up to 600 mg/kg/day. This represents an exposure of about two and six times the maximum recommended human daily dose of 2000 mg based on body surface area comparisons for rats and rabbits, respectively. Determination of fetal concentrations demonstrated a partial placental barrier to metformin.

Nursing Mothers

Studies in lactating rats show that metformin is excreted into milk and reaches levels comparable to those in plasma. Similar studies have not been conducted in nursing mothers. Because the potential for hypoglycemia in nursing infants may exist, a decision should be made whether to discontinue nursing or to discontinue the drug, taking into account the importance of the drug to the mother. If metformin hydrochloride extended release tablets USP is discontinued, and if diet alone is inadequate for controlling blood glucose, insulin therapy should be considered.

Pediatric Use

Safety and effectiveness of metformin hydrochloride extended release tablets USP in pediatric patients have not been established.

Geriatric Use

Controlled clinical studies of metformin hydrochloride did not include sufficient numbers of elderly patients to determine whether they respond differently from younger patients, although other reported clinical experience has not identified differences in responses between the elderly and younger patients. Metformin is known to be substantially excreted by the kidney and because the risk of serious adverse reactions to the drug is greater in patients with impaired renal function, metformin hydrochloride should only be used in patients with normal renal function (see Error! Hyperlink reference not valid.Error! Hyperlink reference not valid., and Error! Hyperlink reference not valid.). Because aging is associated with reduced renal function, metformin hydrochloride extended release tablets USP should be used with caution as age increases. Care should be taken in dose selection and should be based on careful and regular monitoring of renal function. Generally, elderly patients should not be titrated to the maximum dose of metformin hydrochloride extended release tablets USP (see also Error! Hyperlink reference not valid. and Error! Hyperlink reference not valid.).

ADVERSE REACTIONS

In worldwide clinical trials over 900 patients with type 2 diabetes have been treated with metformin hydrochloride extended release tablets USP in placebo- and active-controlled studies. In placebo-controlled trials, 781 patients were administered metformin hydrochloride extended release tablets USP and 195 patients received placebo. Adverse reactions reported in greater than 5% of the metformin hydrochloride extended release tablets USP patients, and that were more common in metformin hydrochloride extended release tablets USP - than placebo-treated patients, are listed in Table 12.

Table 12: Most Common Adverse Reactions (>5.0 Percent) in Placebo-Controlled Studies of Metformin Hydrochloride Extended Release Tablets USP*
 | Metformin Hydrochloride Extended Release Tablets USP (n=781) | Placebo (n=195)
Adverse Reaction | % of Patients
Diarrhea | 9.6 | 2.6
Nausea/Vomiting | 6.5 | 1.5
*Reactions that were more common in metformin hydrochloride extended release tablets USP - than placebo-treated patients.

Diarrhea led to discontinuation of study medication in 0.6% of patients treated with metformin hydrochloride extended release tablets USP. Additionally, the following adverse reactions were reported in ≥1.0% - ≤5.0% of metformin hydrochloride extended release tablets USP patients and were more commonly reported with metformin hydrochloride extended release tablets USP than placebo: abdominal pain, constipation, distention abdomen, dyspepsia/heartburn, flatulence, dizziness, headache, upper respiratory infection, taste disturbance.

OVERDOSAGE

Overdose of metformin hydrochloride has occurred, including ingestion of amounts greater than 50 grams. Hypoglycemia was reported in approximately 10% of cases, but no causal association with metformin hydrochloride has been established. Lactic acidosis has been reported in approximately 32% of metformin overdose cases (see Error! Hyperlink reference not valid.). Metformin is dialyzable with a clearance of up to 170 mL/min under good hemodynamic conditions. Therefore, hemodialysis may be useful for removal of accumulated drug from patients in whom metformin overdosage is suspected.

DOSAGE AND ADMINISTRATION

There is no fixed dosage regimen for the management of hyperglycemia in patients with type 2 diabetes with metformin hydrochloride extended release tablets USP or any other pharmacologic agent. Dosage of metformin hydrochloride extended release tablets USP must be individualized on the basis of both effectiveness and tolerance, while not exceeding the maximum recommended daily doses. The maximum recommended daily dose of metformin hydrochloride extended release tablets USP in adults is 2000 mg.

Metformin hydrochloride extended release tablets USP should generally be given once daily with the evening meal. Metformin hydrochloride extended release tablets USP should be started at a low dose, with gradual dose escalation, both to reduce gastrointestinal side effects and to permit identification of the minimum dose required for adequate glycemic control of the patient.

During treatment initiation and dose titration (see Error! Hyperlink reference not valid.), fasting plasma glucose should be used to determine the therapeutic response to metformin hydrochloride extended release tablets USP and identify the minimum effective dose for the patient. Thereafter, glycosylated hemoglobin should be measured at intervals of approximately three months. The therapeutic goal should be to decrease both fasting plasma glucose and glycosylated hemoglobin levels to normal or near normal by using the lowest effective dose of metformin hydrochloride extended release tablets USP, either when used as monotherapy or in combination with sulfonylurea or insulin.

Monitoring of blood glucose and glycosylated hemoglobin will also permit detection of primary failure, i.e., inadequate lowering of blood glucose at the maximum recommended dose of medication, and secondary failure, i.e., loss of an adequate blood glucose lowering response after an initial period of effectiveness.

Short-term administration of metformin hydrochloride extended release tablets USP may be sufficient during periods of transient loss of control in patients usually well-controlled on diet alone.

Metformin hydrochloride extended release tablets USP must be swallowed whole and never crushed or chewed. Occasionally, the inactive ingredients of metformin hydrochloride extended release tablets USP will be eliminated in the feces as a soft, hydrated mass. (See Error! Hyperlink reference not valid. printed below.)

Recommended Dosing Schedule

Adults - In general, clinically significant responses are not seen at doses below 1500 mg per day. However, a lower recommended starting dose and gradually increased dosage is advised to minimize gastrointestinal symptoms.

The usual starting dose of metformin hydrochloride extended release tablets USP is 500 mg once daily with the evening meal. Dosage increases should be made in increments of 500 mg weekly, up to a maximum of 2000 mg once daily with the evening meal. If glycemic control is not achieved on metformin hydrochloride extended release tablets 2000 mg once daily, a trial of metformin hydrochloride extended release tablets 1000 mg twice daily should be considered. If higher doses of metformin are required, metformin hydrochloride tablets should be used at total daily doses up to 2550 mg administered in divided daily doses, as described above. (See Error! Hyperlink reference not valid.)

In a randomized trial, patients currently treated with metformin hydrochloride tablets were switched to metformin hydrochloride extended release tablets USP. Results of this trial suggest that patients receiving metformin hydrochloride tablets treatment may be safely switched to metformin hydrochloride extended release tablets USP once daily at the same total daily dose, up to 2000 mg once daily. Following a switch from metformin hydrochloride tablets to metformin hydrochloride extended release tablets USP, glycemic control should be closely monitored and dosage adjustments made accordingly (see Error! Hyperlink reference not valid.).

Pediatrics - Safety and effectiveness of metformin hydrochloride extended release tablets USP in pediatric patients have not been established.

Transfer From Other Antidiabetic Therapy

When transferring patients from standard oral hypoglycemic agents other than chlorpropamide to metformin hydrochloride extended release tablets USP, no transition period generally is necessary. When transferring patients from chlorpropamide, care should be exercised during the first two weeks because of the prolonged retention of chlorpropamide in the body, leading to overlapping drug effects and possible hypoglycemia.

Concomitant Metformin Hydrochloride Extended Release Tablets USP and Oral Sulfonylurea Therapy in Adult Patients

If patients have not responded to four weeks of the maximum dose of metformin hydrochloride extended release tablets USP monotherapy, consideration should be given to gradual addition of an oral sulfonylurea while continuing metformin hydrochloride extended release tablets USP at the maximum dose, even if prior primary or secondary failure to a sulfonylurea has occurred. Clinical and pharmacokinetic drug-drug interaction data are currently available only for metformin plus glyburide (glibenclamide).

With concomitant metformin hydrochloride extended release tablets USP and sulfonylurea therapy, the desired control of blood glucose may be obtained by adjusting the dose of each drug. However, attempts should be made to identify the minimum effective dose of each drug to achieve this goal. With concomitant metformin hydrochloride extended release tablets USP and sulfonylurea therapy, the risk of hypoglycemia associated with sulfonylurea therapy continues and may be increased. Appropriate precautions should be taken. (See Package Insert of the respective sulfonylurea.)

If patients have not satisfactorily responded to one to three months of concomitant therapy with the maximum dose of metformin hydrochloride extended release tablets USP and the maximum dose of an oral sulfonylurea, consider therapeutic alternatives including switching to insulin with or without metformin hydrochloride extended release tablets USP.

Concomitant Metformin Hydrochloride Extended Release Tablets USP and Insulin Therapy in Adult Patients

The current insulin dose should be continued upon initiation of metformin hydrochloride extended release tablets USP therapy. Metformin hydrochloride extended release tablets USP therapy should be initiated at 500 mg once daily in patients on insulin therapy. For patients not responding adequately, the dose of metformin hydrochloride extended release tablets USP should be increased by 500 mg after approximately 1 week and by 500 mg every week thereafter until adequate glycemic control is achieved. The maximum recommended daily dose is 2000 mg for metformin hydrochloride extended release tablets USP. It is recommended that the insulin dose be decreased by 10% to 25% when fasting plasma glucose concentrations decrease to less than 120 mg/dL in patients receiving concomitant insulin and metformin hydrochloride extended release tablets USP. Further adjustment should be individualized based on glucose-lowering response.

Specific Patient Populations

Metformin hydrochloride extended release tablets USP is not recommended for use in pregnancy. Metformin hydrochloride extended-release tablets USP is not recommended in pediatric patients (below the age of 17 years).

The initial and maintenance dosing of metformin hydrochloride extended release tablets USP should be conservative in patients with advanced age, due to the potential for decreased renal function in this population. Any dosage adjustment should be based on a careful assessment of renal function. Generally, elderly, debilitated, and malnourished patients should not be titrated to the maximum dose of metformin hydrochloride extended release tablets USP.

Monitoring of renal function is necessary to aid in prevention of lactic acidosis, particularly in the elderly. (See Error! Hyperlink reference not valid..)

HOW SUPPLIED

Metformin Hydrochloride Extended Release Tablets USP

500 mg Bottles of 30 NDC 63187-779-30

500 mg Bottles of 60 NDC 63187-779-60

500 mg Bottles of 90 NDC 63187-779-90

500 mg Bottles of 180 NDC 63187-779-78

Metformin hydrochloride extended release tablets USP 500 mg are white to off-white, capsule shaped, biconvex, beveled edge tablet, with occasionally mottled appearance, debossed with "˥L 001" on one side and plain on other side.

Storage

Store at 20° to 25° C (68° to 77° F); excursions permitted to 15° to 30° C (59° to 86° F). (See USP Controlled Room Temperature.)

Dispense in light-resistant containers.

Manufactured By:

Inventia Healthcare Private Limited

Plot No.F1 & F-1/1, Additional Ambernath M.I.D.C.,

Ambernath (East)-421506,

Dist. Thane, Maharashtra, India

Distributed by:

Ascend Laboratories, LLC Montvale,

NJ 07645

Repackaged by:

Proficient Rx LP

Thousand Oaks, CA 91320

PT 1977

What are the side effects of metformin hydrochloride extended release tablets USP?

Lactic Acidosis. In rare cases, metformin hydrochloride can cause a serious side effect called lactic acidosis. This is caused by a buildup of lactic acid in your blood. This buildup can cause serious damage. Lactic acidosis caused by metformin hydrochloride is rare and has occurred mostly in people whose kidneys were not working normally. Lactic acidosis has been reported in about one in 33,000 patients taking metformin hydrochloride over the course of a year. Although rare, if lactic acidosis does occur, it can be fatal in up to half the people who develop it.

It is also important for your liver to be working normally when you take metformin hydrochloride extended release tablets USP. Your liver helps remove lactic acid from your blood.

Make sure you tell your doctor before you use metformin hydrochloride extended release tablets USP if you have kidney or liver problems. You should also stop using metformin hydrochloride extended release tablets USP and call your doctor right away if you have signs of lactic acidosis. Lactic acidosis is a medical emergency that must be treated in a hospital.

Signs of lactic acidosis are:

- feeling very weak, tired, or uncomfortable
- unusual muscle pain
- trouble breathing
- unusual or unexpected stomach discomfort
- feeling cold
- feeling dizzy or lightheaded
- suddenly developing a slow or irregular heartbeat

If your medical condition suddenly changes, stop taking metformin hydrochloride extended release tablets USP and call your doctor right away. This may be a sign of lactic acidosis or another serious side effect.

Other Side Effects. Common side effects of metformin hydrochloride include diarrhea, nausea, and upset stomach. These side effects generally go away after you take the medicine for a while. Taking your medicine with meals can help reduce these side effects. Tell your doctor if the side effects bother you a lot, last for more than a few weeks, come back after they’ve gone away, or start later in therapy. You may need a lower dose or need to stop taking the medicine for a short period or for good.

About 3 out of every 100 people who take metformin hydrochloride extended release tablets USP have an unpleasant metallic taste when they start taking the medicine. It lasts for a short time.

Metformin hydrochloride extended release tablets USP rarely cause hypoglycemia (low blood sugar) by themselves. However, hypoglycemia can happen if you do not eat enough, if you drink alcohol, or if you take other medicines to lower blood sugar.

General advice about prescription medicines

If you have questions or problems, talk with your doctor or other healthcare provider. You can ask your doctor or pharmacist for the information about metformin hydrochloride that is written for health care professionals. Medicines are sometimes prescribed for purposes other than those listed in a patient information leaflet. Do not use metformin hydrochloride extended release tablets USP for a condition for which it was not prescribed. Do not share your medicine with other people.

Manufactured By:

Inventia Healthcare Private Limited

Plot No.F1 & F-1/1, Additional Ambernath M.I.D.C.,

Ambernath (East)-421506,

Dist. Thane, Maharashtra, India

Distributed by:

Ascend Laboratories, LLC Montvale,

NJ 07645

Repackaged by:

Proficient Rx LP

Thousand Oaks, CA 91320

PATIENT INFORMATION

Metformin Hydrochloride Extended Release Tablets USP

Rx only

Read this information carefully before you start taking this medicine and each time you refill your prescription. There may be new information. This information does not take the place of your doctor’s advice. Ask your doctor or pharmacist if you do not understand some of this information or if you want to know more about this medicine.

What are metformin hydrochloride extended release tablets USP?

Metformin hydrochloride is used to treat type 2 diabetes. This is also known as non-insulin-dependent diabetes mellitus. People with type 2 diabetes are not able to make enough insulin or respond normally to the insulin their bodies make. When this happens, sugar (glucose) builds up in the blood. This can lead to serious medical problems including kidney damage, amputations, and blindness. Diabetes is also closely linked to heart disease. The main goal of treating diabetes is to lower your blood sugar to a normal level.

High blood sugar can be lowered by diet and exercise, by a number of medicines taken by mouth, and by insulin shots. Before you take metformin hydrochloride extended release tablets USP, try to control your diabetes by exercise and weight loss. While you take your diabetes medicine, continue to exercise and follow the diet advised for your diabetes. No matter what your recommended diabetes management plan is, studies have shown that maintaining good blood sugar control can prevent or delay complications of diabetes, such as blindness.

Metformin hydrochloride extended release tablets USP works longer in your body. Both of these medicines help control your blood sugar in a number of ways. These include helping your body respond better to the insulin it makes naturally, decreasing the amount of sugar your liver makes, and decreasing the amount of sugar your intestines absorb. Metformin hydrochloride extended release tablets USP do not cause your body to make more insulin. Because of this, when taken alone, they rarely cause hypoglycemia (low blood sugar), and usually do not cause weight gain. However, when they are taken with a sulfonylurea or with insulin, hypoglycemia is more likely to occur, as is weight gain.

WARNING: A small number of people who have metformin hydrochloride have developed a serious condition called lactic acidosis. Lactic acidosis is caused by a buildup of lactic acid in the blood. This happen more often in people with kidney problems. Most people with kidney problems should not take metformin hydrochloride extended release tablets USP. (See "Error! Hyperlink reference not valid.")

Who should not take metformin hydrochloride extended release tablets USP?

Some conditions increase your chance of getting lactic acidosis, or cause other problems if you take either of these medicines. Most of the conditions listed below can increase your chance of getting lactic acidosis.

Do not take metformin hydrochloride extended release tablets USP if you:

- have kidney problems
- have liver problems
- have heart failure that is treated with medicines, such as Lanoxin® (digoxin) or Lasix® (furosemide)
- drink a lot of alcohol. This means you binge drink for short periods or drink all the time
- are seriously dehydrated (have lost a lot of water from your body)
- are going to have an x-ray procedure with injection of dyes (contrast agents)
- are going to have surgery
- develop a serious condition, such as heart attack, severe infection, or a stroke
- are 80 years or older and you have NOT had your kidney function tested

Tell your doctor if you are pregnant or plan to become pregnant. Metformin hydrochloride extended release tablets USP may not be right for you. Talk with your doctor about your choices. You should also discuss your choices with your doctor if you are nursing a child.

Can metformin hydrochloride extended release tablets USP be used in children?

Metformin hydrochloride extended release tablets USP have not been studied in children.

How should I take metformin hydrochloride extended release tablets USP?

Your doctor will tell you how much medicine to take and when to take it. You will probably start out with a low dose of the medicine. Your doctor may slowly increase your dose until your blood sugar is better controlled. You should take metformin hydrochloride extended release tablets USP with meals.

Your doctor may have you take other medicines along with metformin hydrochloride extended release tablets USP to control your blood sugar. These medicines may include insulin shots. Taking metformin hydrochloride extended release tablets USP with insulin may help you better control your blood sugar while reducing the insulin dose.

Continue your exercise and diet program and test your blood sugar regularly while taking metformin hydrochloride extended release tablets USP. Your doctor will monitor your diabetes and may perform blood tests on you from time to time to make sure your kidneys and your liver are functioning normally. There is no evidence that metformin hydrochloride extended release tablets USP causes harm to the liver or kidneys.

Tell your doctor if you:

- have an illness that causes severe vomiting, diarrhea or fever, or if you drink a much lower amount of liquid than normal. These conditions can lead to severe dehydration (loss of water in your body).You may need to stop taking metformin hydrochloride extended release tablets USP for a short time.
- plan to have surgery or an x-ray procedure with injection of dye (contrast agent). You may need to stop taking metformin hydrochloride extended release tablets USP for a short time.
- start to take other medicines or change how you take a medicine. Metformin hydrochloride can affect how well other drugs work, and some drugs can affect how well metformin hydrochloride work. Some medicines may cause high blood sugar.

Metformin hydrochloride extended release tablets USP must be swallowed whole and never crushed or chewed. Occasionally, the inactive ingredients of metformin hydrochloride extended release tablets USP may be eliminated as a soft mass in your stool that may look like the original tablet; this is not harmful and will not affect the way metformin hydrochloride extended release tablets USP works to control your diabetes.

What should I avoid while taking metformin hydrochloride extended release tablets USP?

Do not drink a lot of alcoholic drinks while taking metformin hydrochloride extended release tablets USP. This means you should not binge drink for short periods, and you should not drink a lot of alcohol on a regular basis. Alcohol can increase the chance of getting lactic acidosis.

PACKAGE LABEL

NDC 63187-779-90

90 Tablets

Metformin Hydrochloride
Extended Release Tablets USP

500 mg

PHARMACIST: Dispense with a patient
information leaflet.

Rx only